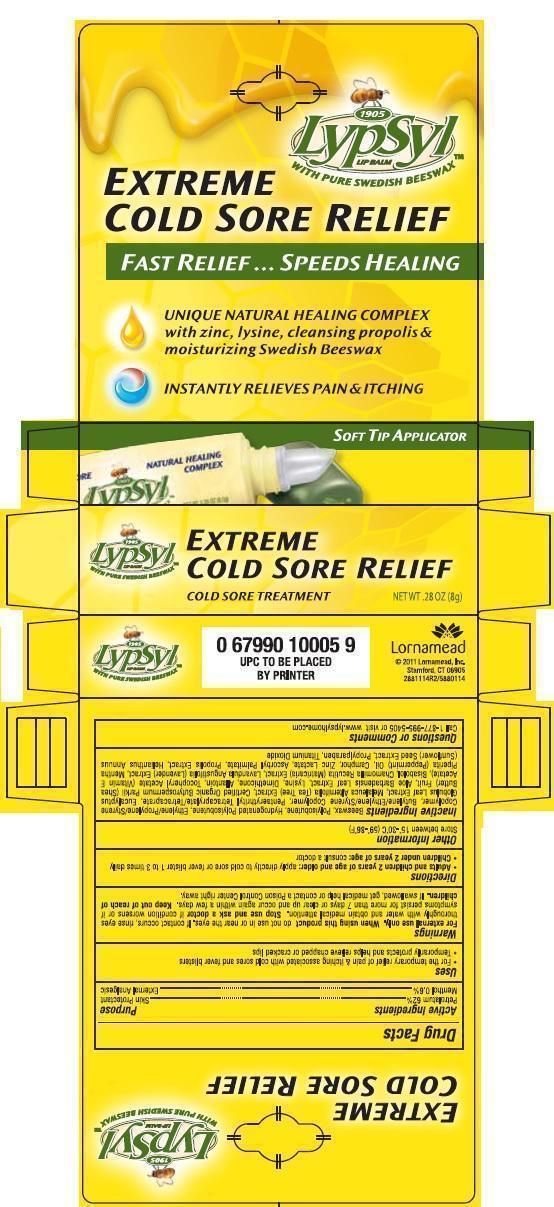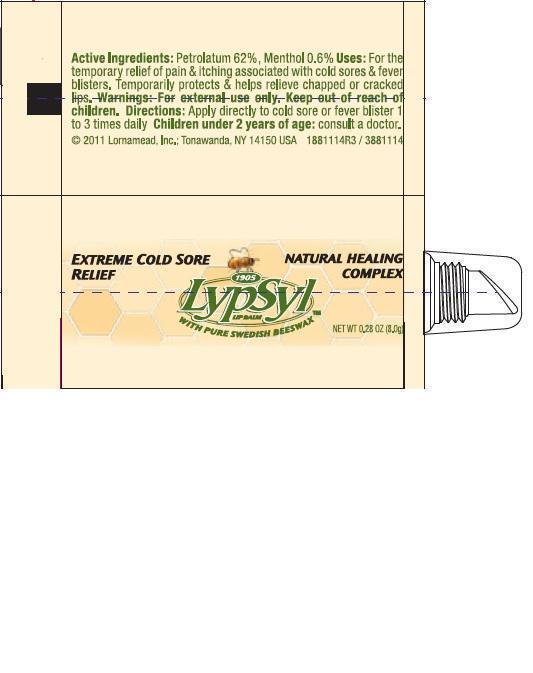 DRUG LABEL: Lornamead
NDC: 62721-8114 | Form: PASTE
Manufacturer: Lornamead
Category: otc | Type: HUMAN OTC DRUG LABEL
Date: 20130306

ACTIVE INGREDIENTS: PETROLATUM 65.004 g/100 g; MENTHOL 0.3 g/100 g
INACTIVE INGREDIENTS: PROPYLPARABEN; ALLANTOIN; SHEA BUTTER; YELLOW WAX; DIMETHICONE; PENTAERYTHRITYL TETRACAPRYLATE/TETRACAPRATE; POLYISOBUTYLENE (2300 MW); ALOE VERA LEAF; LEVOMENOL; .ALPHA.-TOCOPHEROL ACETATE; JOJOBA OIL; LAVANDULA ANGUSTIFOLIA FLOWER; CHAMOMILE; TITANIUM DIOXIDE; LYSINE; HELIANTHUS ANNUUS FLOWERING TOP; ZINC LACTATE; ASCORBYL PALMITATE; EUCALYPTUS GLOBULUS LEAF; CAMPHOR (NATURAL); MELALEUCA ALTERNIFOLIA LEAF; MENTHA PIPERITA

Drug Facts

Active ingredients

Petrolatum 62% ......................................................... Skin Protectant

Menthol 0.6% .............................................................External Analgesic

Uses

- For the temporary relief of pain & itching associated with cold sores and fever blisters
- Temporarily protects and helps relieve chapped or cracked lips

WARNINGS

For External Use Only. When using this product do not use in or near the eyes. If contact occurs, rinse eyes thoroughly with water and obtain medical attention. Stop use and ask a doctor if condition worsens or if symptoms persist for more than 7 days or clear up and occur again within a few days.

Keep out of reach of children. If swallowed, get medical help or contact a Poison Control Center right away.

Directions

Adults and children 12 years of age and older: Apply directly to cold sore or fever blister 1 to 3 times daily

Children under 2 years of age: Consult a doctor

DOSAGE AND ADMINISTRATION

Apply directly to cold sore or fever blister 1 to 3 times daily Children under 2 years of age: ask a doctor

Other Information

Store between 15 - 30C (59-86F)

Inactive ingredients

Beeswax, Polyisobutene, Hydrogenatede Polyisobutene, Ethylene/Propylene/Styrene Copolymer, Butylene/Ethylene/Styrene Copolymer, Pentaerythrityl Tetracaprylate/Tetracaprate, Eucalyptus Globulus Leaf Extract, Melaleuca Alternifolia (Tea Tree) Extract, Ceretified Organic Butyrospermum Parkii (Shea Butter) Fruit, Aloe Barbadensis Leaf Extract, Lysine, Dimethicone, Allantoin, Tocopheryl Acetate (Vitamin E Acetate), Bisabolol, Chamomilla Recutita (Matricaria) Extract, Lavandula Angustifolia (Lavender) Extract, Mentha Piperita (Peppermint) Oil, Camphor, Zinc Lactate, Ascorbyl Palmitate, Propolis Extract, Helianthus Annuus (Sunflower) Seed Extract, Propylparaben, Titanium Dioxide

PACKAGE LABEL

mm1.jpg

mm2.jpg